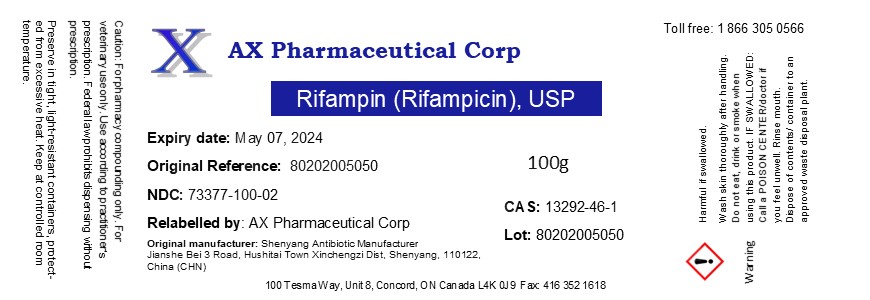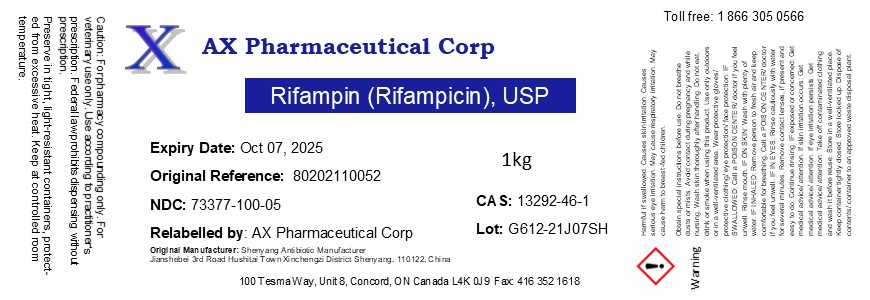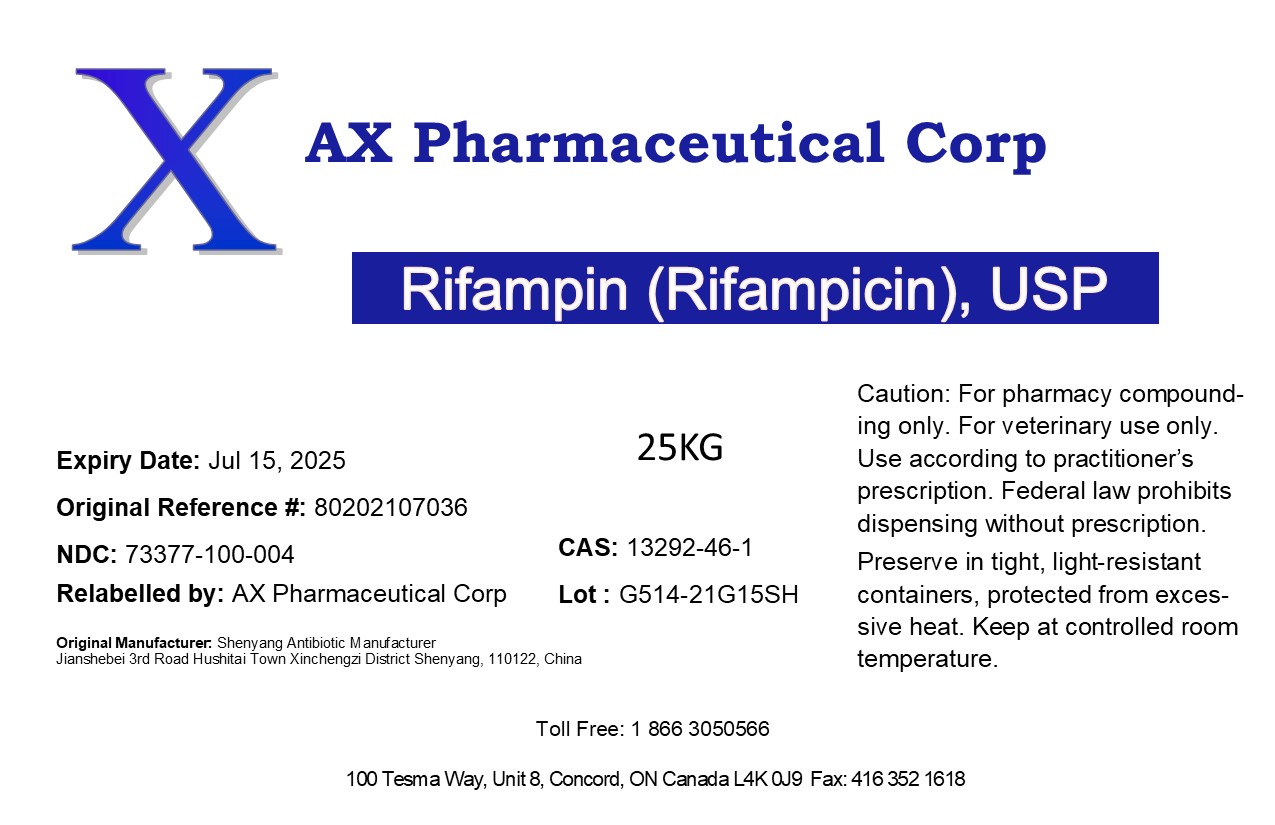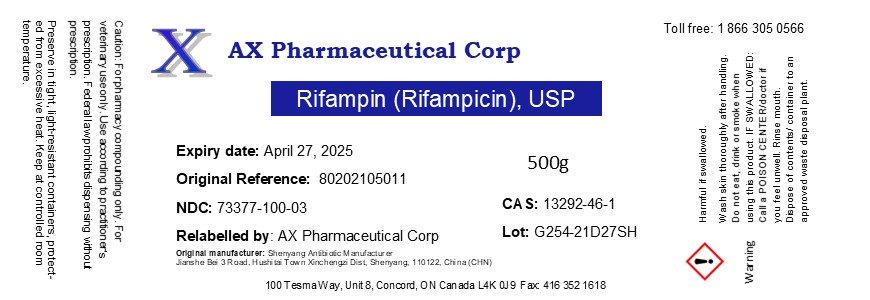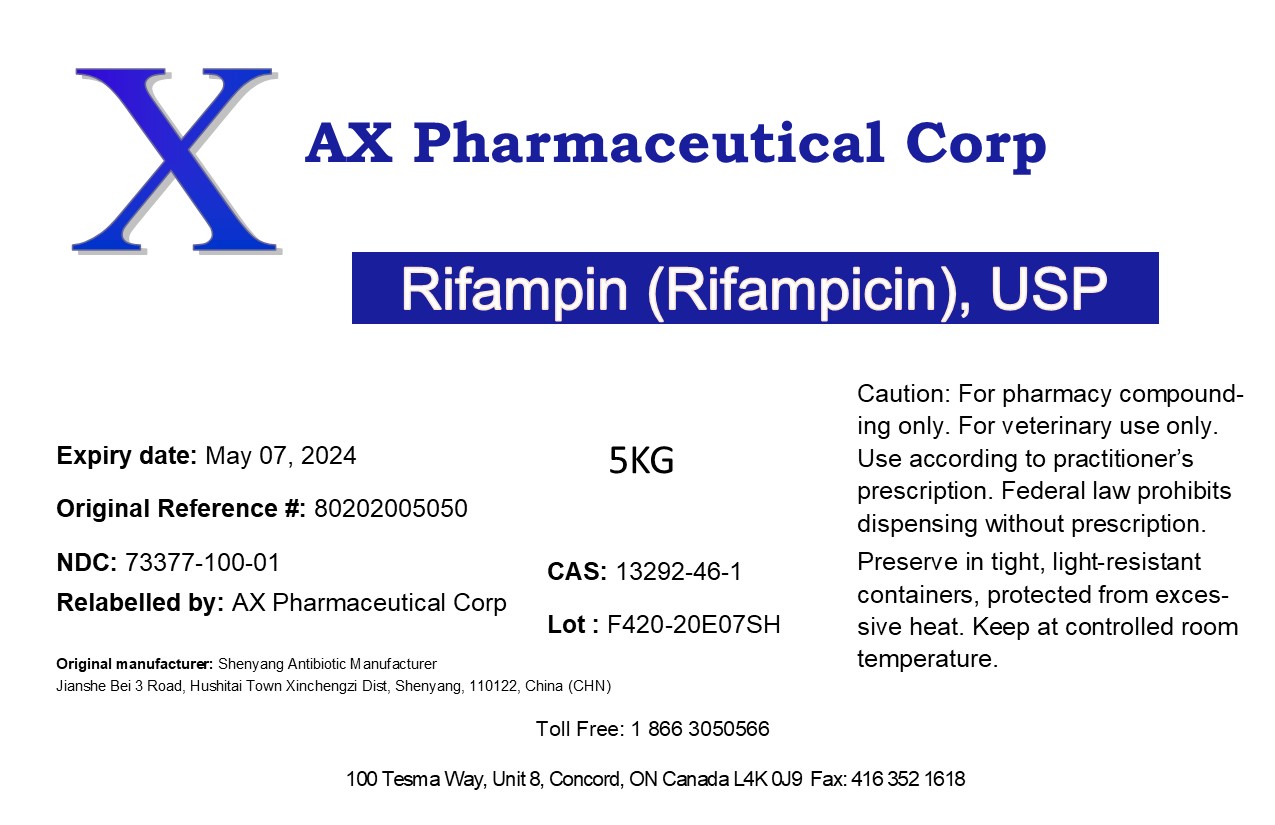 DRUG LABEL: Rifampin (Rifampicin)
NDC: 73377-100 | Form: POWDER
Manufacturer: AX Pharmaceutical Corp
Category: other | Type: BULK INGREDIENT
Date: 20211124

ACTIVE INGREDIENTS: RIFAMPIN 1 kg/1 kg

Rifampin (Rifampicin)